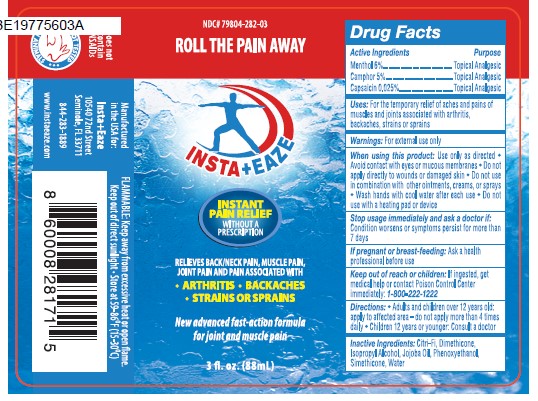 DRUG LABEL: Pain Relief Roll On
NDC: 79804-282 | Form: LIQUID
Manufacturer: Eagle Labs Inc
Category: otc | Type: HUMAN OTC DRUG LABEL
Date: 20260114

ACTIVE INGREDIENTS: MENTHOL 0.06 g/1 g; CAMPHOR (SYNTHETIC) 0.05 g/1 g; CAPSAICIN 0.00025 g/1 g
INACTIVE INGREDIENTS: PHENOXYETHANOL; JOJOBA OIL; DIMETHICONE; ISOPROPYL ALCOHOL; WATER; SILICON DIOXIDE; CITRUS FRUIT

Pain Relief Roll On

Active Ingredient

Menthol 6%

Camphor 5%

Capsaicin 0.025%

Purpose

Topical Analgesic

Uses:

For the temporary relief of aches and pains of muscles and joints associated with arthritis, backaches, strains or sprains

Warnings

For External use only

When using this product

Use only as directed. Avoid contact with eyes or mucous membranes. Do not apply directly to wounds or damaged skin. Do not use in combination with other ointments, creams, or sprays. Wash hand with cool water after each uyse. Do not use with a heating pad or device.

Stop usage immediately and ask a doctor if:

Condition worsens or symptoms persist for more than 7 days

If pregnant or breast-feeding:

Ask a health professional before use

Keep out of reach of children:

If ingested get medical help or contact Poison control center immediately: 1-800-222-1222

Directions:

Adults and Children over 12 years old: Apply to afected area - do not apply more than 4 times daily. Children 12 years or younger: consult a doctor

Inactive Ingredients

Citrus Fiber, Dimethicone, Isopropyl Alcohol, Jojoba Oil, Phenoxyethanol, Simethicone, Water